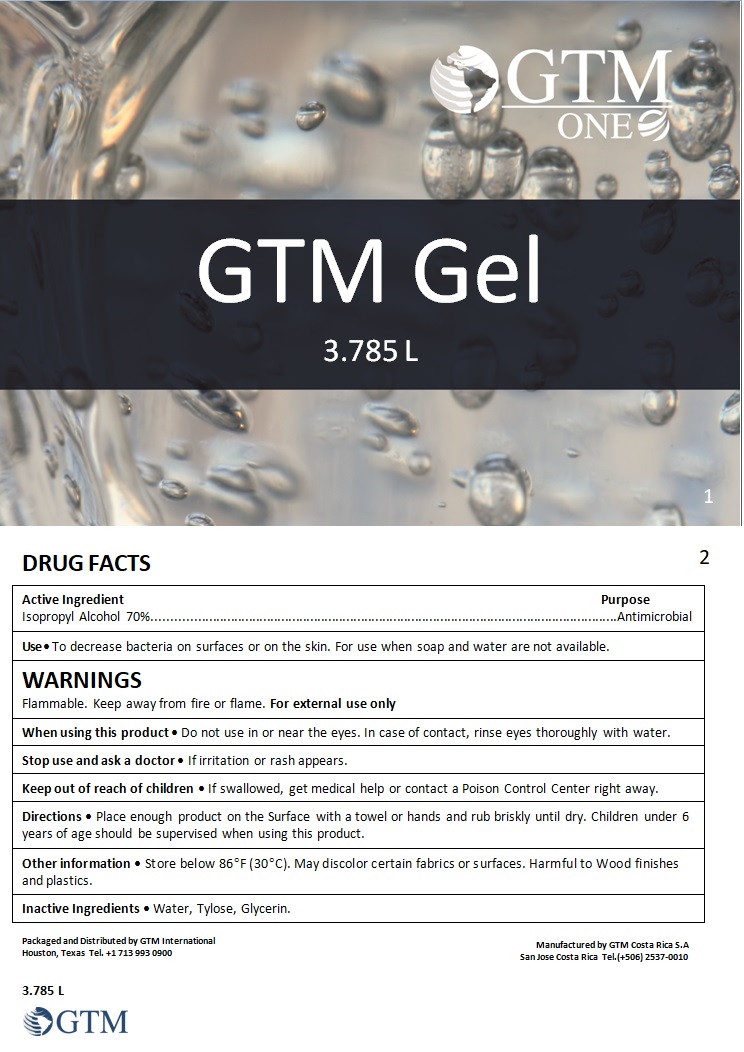 DRUG LABEL: GTM Gel
NDC: 79859-001 | Form: GEL
Manufacturer: GTM Costa Rica Sociedad Anonima
Category: otc | Type: HUMAN OTC DRUG LABEL
Date: 20200810

ACTIVE INGREDIENTS: ISOPROPYL ALCOHOL 0.7 mL/1 mL
INACTIVE INGREDIENTS: WATER; TYLOSEMA ESCULENTUM WHOLE; GLYCERIN

GTM Gel

Active Ingredient

Isopropyl Alcohol 70%

Purpose

Antimicrobial

Use

To decrease bacteria on surfaces or on the skin. For use when soap and water are not available.

WARNINGS

Flammable. Keep away from fire or flame. For external use only

When using this product

• Do not use in or near the eyes. In case of contact, rinse eyes thoroughly with water.

Stop use and ask a doctor

• If irritation or rash appears.

Keep out of reach of children

• If swallowed, get medical help or contact a Poison Control Center right away.

Directions

• Place enough product on the Surface with a towel or hands and rub briskly until dry. Children under 6 years of age should be supervised when using this product

Other information

• Store below 86°F (30°C). May discolor certain fabrics or surfaces. Harmful to Wood finishes and plastics.

Inactive Ingredients

• Water, Tylose, Glycerin.